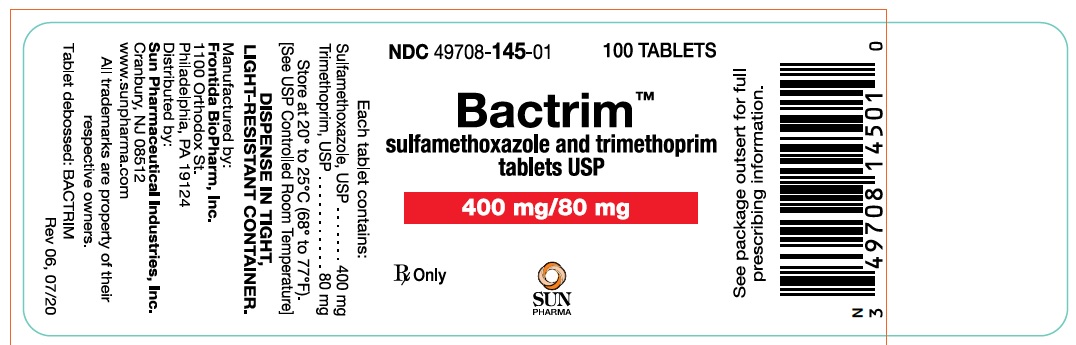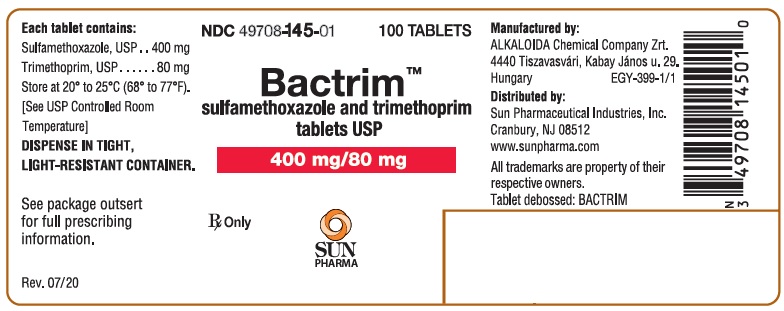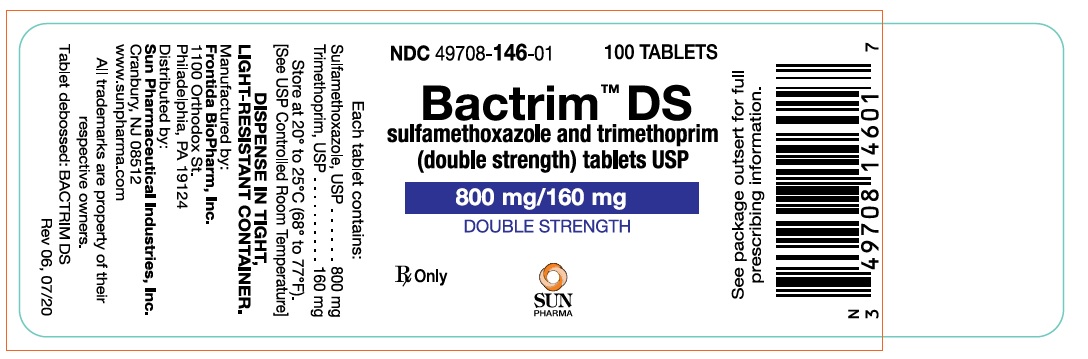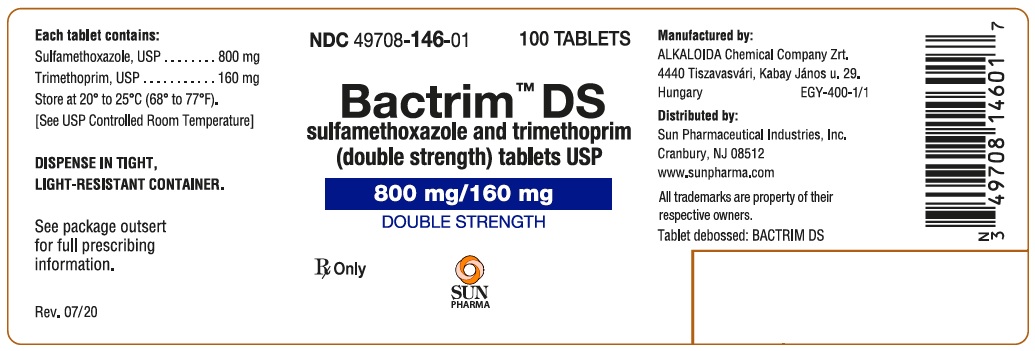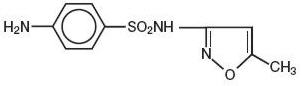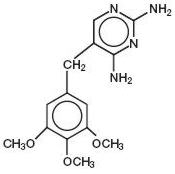 DRUG LABEL: Bactrim DS
NDC: 49708-146 | Form: TABLET
Manufacturer: Sun Pharmaceutical Industries, Inc
Category: prescription | Type: HUMAN PRESCRIPTION DRUG LABEL
Date: 20241230

ACTIVE INGREDIENTS: SULFAMETHOXAZOLE 800 mg/1 1; TRIMETHOPRIM 160 mg/1 1
INACTIVE INGREDIENTS: DOCUSATE SODIUM; SODIUM BENZOATE; SODIUM STARCH GLYCOLATE TYPE A POTATO; MAGNESIUM STEARATE; STARCH, CORN

BACTRIM™
sulfamethoxazole and trimethoprim DS
(double strength) tablets and tablets USP

Rx only

To reduce the development of drug-resistant bacteria and maintain the effectiveness of BACTRIM (sulfamethoxazole and trimethoprim) tablets and other antibacterial drugs, BACTRIM (sulfamethoxazole and trimethoprim) tablets should be used only to treat or prevent infections that are proven or strongly suspected to be caused by bacteria.

DESCRIPTION

BACTRIM (sulfamethoxazole and trimethoprim) is a synthetic antibacterial combination product available in DS (double strength) tablets, each containing 800 mg sulfamethoxazole and 160 mg trimethoprim; in tablets, each containing 400 mg sulfamethoxazole and 80 mg trimethoprim for oral administration.

Sulfamethoxazole is N^1-(5-methyl-3-isoxazolyl) sulfanilamide; the molecular formula is C10H11N3O3S. It is an almost white, odorless, tasteless compound with a molecular weight of 253.28 and the following structural formula:

Trimethoprim is 2,4-diamino-5-(3,4,5-trimethoxybenzyl) pyrimidine; the molecular formula is C14H18N4O3. It is a white to light yellow, odorless, bitter compound with a molecular weight of 290.3 and the following structural formula:

Inactive ingredients:Docusate sodium 85%, sodium benzoate 15%, sodium starch glycolate, magnesium stearate and pregelatinized starch.

CLINICAL PHARMACOLOGY

BACTRIM is rapidly absorbed following oral administration. Both sulfamethoxazole and trimethoprim exist in the blood as unbound, protein-bound and metabolized forms; sulfamethoxazole also exists as the conjugated form. Sulfamethoxazole is metabolized in humans to at least 5 metabolites: the N4-acetyl-, N4-hydroxy-, 5-methylhydroxy-, N4-acetyl-5-methylhydroxy- sulfamethoxazole metabolites, and an N-glucuronide conjugate. The formulation of N4-hydroxy metabolite is mediated viaCYP2C9.

Trimethoprim is metabolized in vitroto 11 different metabolites, of which, five are glutathione adducts and six are oxidative metabolites, including the major metabolites, 1- and 3-oxides and the 3- and 4-hydroxy derivatives.

The free forms of sulfamethoxazole and trimethoprim are considered to be the therapeutically active forms.

In vitrostudies suggest that trimethoprim is a substrate of P-glycoprotein, OCT1 and OCT2, and that sulfamethoxazole is not a substrate of P-glycoprotein.

Approximately 70% of sulfamethoxazole and 44% of trimethoprim are bound to plasma proteins. The presence of 10 mg percent sulfamethoxazole in plasma decreases the protein binding of trimethoprim by an insignificant degree; trimethoprim does not influence the protein binding of sulfamethoxazole.

Peak blood levels for the individual components occur 1 to 4 hours after oral administration. The mean serum half-lives of sulfamethoxazole and trimethoprim are 10 and 8 to 10 hours, respectively. However, patients with severely impaired renal function exhibit an increase in the half-lives of both components, requiring dosage regimen adjustment (see DOSAGE AND ADMINISTRATIONsection). Detectable amounts of sulfamethoxazole and trimethoprim are present in the blood 24 hours after drug administration. During administration of 800 mg sulfamethoxazole and 160 mg trimethoprim b.i.d., the mean steady-state plasma concentration of trimethoprim was 1.72 µg/mL. The steady-state mean plasma levels of free and total sulfamethoxazole were 57.4 µg/mL and 68.0 µg/mL, respectively. These steady-state levels were achieved after three days of drug administration.^1Excretion of sulfamethoxazole and trimethoprim is primarily by the kidneys through both glomerular filtration and tubular secretion. Urine concentrations of both sulfamethoxazole and trimethoprim are considerably higher than are the concentrations in the blood. The average percentage of the dose recovered in urine from 0 to 72 hours after a single oral dose of sulfamethoxazole and trimethoprim is 84.5% for total sulfonamide and 66.8% for free trimethoprim. Thirty percent of the total sulfonamide is excreted as free sulfamethoxazole, with the remaining as N4-acetylated metabolite.^2When administered together as sulfamethoxazole and trimethoprim, neither sulfamethoxazole nor trimethoprim affects the urinary excretion pattern of the other.

Both sulfamethoxazole and trimethoprim distribute to sputum, vaginal fluid and middle ear fluid; trimethoprim also distributes to bronchial secretion, and both pass the placental barrier and are excreted in human milk.

Pharmacokinetics in Pediatric Patients

A simulation conducted with data from a pharmacokinetic study in 153 infants and children demonstrated that mean steady state AUC and maximum plasma concentration of trimethoprim and sulfamethoxazole would be comparable between pediatric patients 2 months to 18 years receiving 8/40 (trimethoprim/ sulfamethoxazole) mg/kg/day divided every 12 hours and adult patients receiving 320/1600 (trimethoprim/ sulfamethoxazole) mg/day.

Pharmacokinetics in Geriatric Patients

The pharmacokinetics of sulfamethoxazole 800 mg and trimethoprim 160 mg were studied in 6 geriatric subjects (mean age: 78.6 years) and 6 young healthy subjects (mean age: 29.3 years) using a non-US approved formulation. Pharmacokinetic values for sulfamethoxazole in geriatric subjects were similar to those observed in young adult subjects. The mean renal clearance of trimethoprim was significantly lower in geriatric subjects compared with young adult subjects (19 mL/h/kg vs. 55 mL/h/kg). However, after normalizing by body weight, the apparent total body clearance of trimethoprim was on average 19% lower in geriatric subjects compared with young adult subjects.^3

Microbiology

Mechanism of Action

Sulfamethoxazole inhibits bacterial synthesis of dihydrofolic acid by competing with para-aminobenzoic acid (PABA). Trimethoprim blocks the production of tetrahydrofolic acid from dihydrofolic acid by binding to and reversibly inhibiting the required enzyme, dihydrofolate reductase. Thus, sulfamethoxazole and trimethoprim blocks two consecutive steps in the biosynthesis of nucleic acids and proteins essential to many bacteria.

Resistance

In vitrostudies have shown that bacterial resistance develops more slowly with both sulfamethoxazole and trimethoprim in combination than with either sulfamethoxazole or trimethoprim alone.

Antimicrobial Activity

BACTRIM has been shown to be active against most isolates of the following microorganisms, both in vitroand in clinical infections as described in the INDICATIONS AND USAGEsection.

Aerobic gram-positive bacteria

Streptococcus pneumoniae

Aerobic gram-negative bacteria

Escherichia coli(including susceptible enterotoxigenic strains implicated in traveler's diarrhea)

Klebsiellaspecies

Enterobacterspecies

Haemophilus influenzae

Morganella morganii

Proteus mirabilis

Proteus vulgaris

Shigella flexneri

Shigella sonnei

Other Microorganisms

Pneumocystis jirovecii

Susceptibility Testing

For specific information regarding susceptibility test interpretive criteria and associated test methods and quality control standards recognized by FDA for this drug, please see: https://www.fda.gov/STIC.

INDICATIONS AND USAGE

To reduce the development of drug-resistant bacteria and maintain the effectiveness of BACTRIM (sulfamethoxazole and trimethoprim) tablets and other antibacterial drugs, BACTRIM (sulfamethoxazole and trimethoprim) tablets should be used only to treat or prevent infections that are proven or strongly suspected to be caused by susceptible bacteria. When culture and susceptibility information are available, they should be considered in selecting or modifying antibacterial therapy. In the absence of such data, local epidemiology and susceptibility patterns may contribute to empiric selection of therapy.

Urinary Tract Infections

For the treatment of urinary tract infections due to susceptible strains of the following organisms: Escherichia coli, Klebsiellaspecies, Enterobacterspecies, Morganella morganii, Proteus mirabilisand Proteus vulgaris. It is recommended that initial episodes of uncomplicated urinary tract infections be treated with a single effective antibacterial agent rather than the combination.

Acute Otitis Media

For the treatment of acute otitis media in pediatric patients due to susceptible strains of Streptococcus pneumoniaeor Haemophilus influenzaewhen in the judgment of the physician sulfamethoxazole and trimethoprim offers some advantage over the use of other antimicrobial agents. To date, there are limited data on the safety of repeated use of BACTRIM in pediatric patients under two years of age. BACTRIM is not indicated for prophylactic or prolonged administration in otitis media at any age.

Acute Exacerbations of Chronic Bronchitis in Adults

For the treatment of acute exacerbations of chronic bronchitis due to susceptible strains of Streptococcus pneumoniaeor Haemophilus influenzaewhen a physician deems that BACTRIM could offer some advantage over the use of a single antimicrobial agent.

Shigellosis

For the treatment of enteritis caused by susceptible strains of Shigella flexneriand Shigella sonneiwhen antibacterial therapy is indicated.

Pneumocystis jiroveciiPneumonia

For the treatment of documented Pneumocystis jiroveciipneumonia and for prophylaxis against P. jiroveciipneumonia in individuals who are immunosuppressed and considered to be at an increased risk of developing P. jiroveciipneumonia.

Traveler's Diarrhea in Adults

For the treatment of traveler's diarrhea due to susceptible strains of enterotoxigenic E. coli.

CONTRAINDICATIONS

BACTRIM is contraindicated in the following situations:

- a known hypersensitivity to trimethoprim or sulfonamides
- history of drug-induced immune thrombocytopenia with use of trimethoprim and/or sulfonamides
- documented megaloblastic anemia due to folate deficiency
- pediatric patients less than 2 months of age
- marked hepatic damage
- severe renal insufficiency when renal function status cannot be monitored
- concomitant administration with dofetilide (see PRECAUTIONS).

WARNINGS

Embryofetal Toxicity

Some epidemiologic studies suggest that exposure to BACTRIM during pregnancy may be associated with an increased risk of congenital malformations, particularly neural tube defects, cardiovascular malformations, urinary tract defects, oral clefts, and club foot. If BACTRIM is used during pregnancy, or if the patient becomes pregnant while taking this drug, the patient should be advised of the potential hazards to the fetus (see PRECAUTIONS).

Hypersensitivity and Other Serious or Fatal Reactions

Fatalities and serious adverse reactions including severe cutaneous adverse reactions (SCARs) including Stevens-Johnson syndrome, toxic epidermal necrolysis, drug reaction with eosinophilia and systemic symptoms (DRESS), acute febrile neutrophilic dermatosis (AFND), acute generalized erythematous pustulosis (AGEP); fulminant hepatic necrosis; agranulocytosis, aplastic anemia and other blood dyscrasias; acute and delayed lung injury; anaphylaxis and circulatory shock have occurred with the administration of sulfamethoxazole and trimethoprim products, including BACTRIM (see ADVERSE REACTIONS).

Hypersensitivity Reactions of the Respiratory Tract

Cough, shortness of breath and pulmonary infiltrates potentially representing hypersensitivity reactions of the respiratory tract have been reported in association with sulfamethoxazole and trimethoprim treatment.

Respiratory Failure

Other severe pulmonary adverse reactions occurring within days to week of BACTRIM initiation and resulting in prolonged respiratory failure requiring mechanical ventilation or extracorporeal membrane oxygenation (ECMO), lung transplantation or death have also been reported in patients and otherwise healthy individuals treated with sulfamethoxazole and trimethoprim products.

Circulatory Shock

Circulatory shock with fever, severe hypotension, and confusion requiring intravenous fluid resuscitation and vasopressors has occurred within minutes to hours of re-challenge with sulfamethoxazole and trimethoprim products, including BACTRIM, in patients with history of recent (days to weeks) exposure to sulfamethoxazole and trimethoprim.

Management of Hypersensitivity Reactions

BACTRIM should be discontinued at the first appearance of skin rash or any sign of a serious adverse reaction. A skin rash may be followed by a more severe reaction, such as Stevens-Johnson syndrome, toxic epidermal necrolysis, DRESS, AFND, AGEP, hepatic necrosis, or serious blood disorders (see PRECAUTIONSand ADVERSE REACTIONS). Clinical signs, such as rash, pharyngitis, fever, arthralgia, cough, chest pain, dyspnea, pallor, purpura or jaundice may be early indications of serious reactions.

Hemophagocytic Lymphohistiocytosis

Cases of hemophagocytic lymphohistiocytosis (HLH) have been reported in patients treated with sulfamethoxazole-trimethoprim. HLH is a life-threatening syndrome of pathologic immune activation characterized by clinical signs and symptoms of extreme systemic inflammation. Signs and symptoms of HLH may include fever, hepatosplenomegaly, rash, lymphadenopathy, neurologic symptoms, cytopenias, high serum ferritin, hypertriglyceridemia, and liver enzyme and coagulation abnormalities. If HLH is suspected, discontinue BACTRIM immediately and institute appropriate management.

Streptococcal Infections and Rheumatic Fever

The sulfonamides should not be used for treatment of group A β-hemolytic streptococcal infections. In an established infection, they will not eradicate the streptococcus and, therefore, will not prevent sequelae such as rheumatic fever.

Thrombocytopenia

BACTRIM-induced thrombocytopenia may be an immune-mediated disorder. Severe cases of thrombocytopenia that are fatal or life threatening have been reported. Thrombocytopenia usually resolves within a week upon discontinuation of BACTRIM.

Clostridioides difficileassociated diarrhea (CDAD) has been reported with use of nearly all antibacterial agents, including BACTRIM, and may range in severity from mild diarrhea to fatal colitis. Treatment with antibacterial agents alters the normal flora of the colon leading to overgrowth of C. difficile.

C. difficileproduces toxins A and B which contribute to the development of CDAD. Hypertoxin producing strains of C. difficilecause increased morbidity and mortality, as these infections can be refractory to antimicrobial therapy and may require colectomy. CDAD must be considered in all patients who present with diarrhea following antibiotic use. Careful medical history is necessary since CDAD has been reported to occur over two months after the administration of antibacterial agents.

If CDAD is suspected or confirmed, ongoing antibiotic use not directed against C. difficilemay need to be discontinued. Appropriate fluid and electrolyte management, protein supplementation, antibiotic treatment of C. difficile, and surgical evaluation should be instituted as clinically indicated.

Risk Associated with Concurrent Use of Leucovorin for Pneumocystis jiroveciiPneumonia

Treatment failure and excess mortality were observed when BACTRIM was used concomitantly with leucovorin for the treatment of HIV positive patients with P. jiroveciipneumonia in a randomized placebo-controlled trial.^4Avoid coadministration of BACTRIM and leucovorin during treatment of P. jiroveciipneumonia.

PRECAUTIONS

Development of Drug Resistant Bacteria

Prescribing BACTRIM (sulfamethoxazole and trimethoprim) tablets in the absence of a proven or strongly suspected bacterial infection or a prophylactic indication is unlikely to provide benefit to the patient and increases the risk of the development of drug-resistant bacteria.

Folate Deficiency

Avoid use of BACTRIM in patients with impaired renal or hepatic function, in those with possible folate deficiency (e.g., the elderly, chronic alcoholics, patients receiving anticonvulsant therapy, patients with malabsorption syndrome, and patients in malnutrition states) and in those with severe allergies or bronchial asthma.

Hematological changes indicative of folic acid deficiency may occur in elderly patients or in patients with preexisting folic acid deficiency or kidney failure. These effects are reversible by folinic acid therapy (see PRECAUTIONS, Geriatric Use).

Hemolysis

In glucose-6-phosphate dehydrogenase deficient individuals, hemolysis may occur. This reaction is frequently dose-related.

Hypoglycemia

Cases of hypoglycemia in non-diabetic patients treated with BACTRIM are seen rarely, usually occurring after a few days of therapy. Patients with renal dysfunction, liver disease, malnutrition or those receiving high doses of BACTRIM are particularly at risk.

Impaired Phenylalanine Metabolism

The trimethoprim component of BACTRIM has been noted to impair phenylalanine metabolism, but this is of no significance in phenylketonuric patients on appropriate dietary restriction.

Porphyria and Hypothyroidism

Like other drugs containing sulfonamides, BACTRIM can precipitate porphyria crisis and hypothyroidism. Avoid use of BACTRIM in patients with porphyria or thyroid dysfunction.

Potential Risk in the Treatment of Pneumocystis jiroveciiPneumonia in Patients with Acquired Immunodeficiency Syndrome (AIDS)

AIDS patients may not tolerate or respond to BACTRIM in the same manner as non-AIDS patients. The incidence of adverse reactions, particularly rash, fever, leukopenia and elevated aminotransferase (transaminase) values, with BACTRIM therapy in AIDS patients who are being treated for P. jiroveciipneumonia has been reported to be increased compared with the incidence normally associated with the use of BACTRIM in non-AIDS patients. If a patient develops skin rash, fever, leukopenia or any sign of adverse reaction, reevaluate benefit-risk of continuing therapy or re-challenge with BACTRIM (see WARNINGS).

Avoid coadministration of BACTRIM and leucovorin during treatment of P. jiroveciipneumonia (see WARNINGS).

Electrolyte Abnormalities

Hyperkalemia: High dosage of trimethoprim, as used in patients with P. jiroveciipneumonia, induces a progressive but reversible increase of serum potassium concentrations in a substantial number of patients. Even treatment with recommended doses may cause hyperkalemia when trimethoprim is administered to patients with underlying disorders of potassium metabolism, with renal insufficiency, or if drugs known to induce hyperkalemia are given concomitantly. Close monitoring of serum potassium is warranted in these patients.

Hyponatremia: Severe and symptomatic hyponatremia can occur in patients receiving BACTRIM, particularly for the treatment of P. jiroveciipneumonia. Evaluation for hyponatremia and appropriate correction is necessary in symptomatic patients to prevent life-threatening complications.

Crystalluria: During treatment, ensure adequate fluid intake and urinary output to prevent crystalluria. Patients who are “slow acetylators” may be more prone to idiosyncratic reactions to sulfonamides.

Information for Patients

Hypersensitivity and Other Serious or Fatal Reactions:Advise patients to stop taking BACTRIM immediately if they experience any clinical signs such as rash, pharyngitis, fever, arthralgia, cough, chest pain, dyspnea, pallor, purpura or jaundice and to contact their healthcare provider as soon as possible (see WARNINGS and ADVERSE REACTIONS).

Antibacterial Resistance:Patients should be counseled that antibacterial drugs including BACTRIM (sulfamethoxazole and trimethoprim) tablets should only be used to treat bacterial infections. They do not treat viral infections (e.g., the common cold). When BACTRIM (sulfamethoxazole and trimethoprim) tablets are prescribed to treat a bacterial infection, patients should be told that although it is common to feel better early in the course of therapy, the medication should be taken exactly as directed. Skipping doses or not completing the full course of therapy may (1) decrease the effectiveness of the immediate treatment and (2) increase the likelihood that bacteria will develop resistance and will not be treatable by BACTRIM (sulfamethoxazole and trimethoprim) tablets or other antibacterial drugs in the future.

Crystalluria and Stone Formation:Advise patients to maintain an adequate fluid intake in order to prevent crystalluria and stone formation.

Diarrhea: Advise patients that diarrhea is a common problem caused by antibiotics which usually ends when the antibiotic is discontinued. Sometimes after starting treatment with antibiotics, patients can develop watery and bloody stools (with or without stomach cramps and fever) even as late as two or more months after having taken the last dose of the antibiotic. If this occurs, patients should contact their physician as soon as possible.

Laboratory Tests

Complete blood counts and clinical chemistry testing should be done frequently in patients receiving BACTRIM. Perform urinalyses with careful microscopic examination and renal function tests during therapy, particularly for those patients with impaired renal function. Discontinue BACTRIM if a significant electrolyte abnormality, renal insufficiency or reduction in the count of any formed blood element is noted.

Drug Interactions

Potential for BACTRIM to Affect Other Drugs

Trimethoprim is an inhibitor of CYP2C8 as well as OCT2 transporter. Sulfamethoxazole is an inhibitor of CYP2C9. Avoid coadministration of BACTRIM with drugs that are substrates of CYP2C8 and 2C9 or OCT2.

Table 1: Drug Interactions with BACTRIM

Drug(s) | Recommendation | Comments
Diuretics | Avoid concurrent use | In elderly patients concurrently receiving certain diuretics, primarily thiazides, an increased incidence of thrombocytopenia with purpura has been reported.
Warfarin | Monitor prothrombin time; and INR | It has been reported that BACTRIM may prolong the prothrombin time in patients who are receiving the anticoagulant warfarin (a CYP2C9 substrate). This interaction should be kept in mind when BACTRIM is given to patients already on anticoagulant therapy, and the coagulation time should be reassessed.
Phenytoin | Monitor serum phenytoin levels | BACTRIM may inhibit the hepatic metabolism of phenytoin (a CYP2C9 substrate). BACTRIM, given at a common clinical dosage, increased the phenytoin half-life by 39% and decreased the phenytoin metabolic clearance rate by 27%.; When administering these drugs concurrently, one should be alert for possible excessive phenytoin effect.
Methotrexate | Avoid concurrent use | Sulfonamides can also displace methotrexate from plasma protein binding sites and can compete with the renal transport of methotrexate, thus increasing free methotrexate concentrations.
Cyclosporine | Avoid concurrent use | There have been reports of marked but reversible nephrotoxicity with coadministration of BACTRIM and cyclosporine in renal transplant recipients.
Digoxin | Monitor serum digoxin levels | Increased digoxin blood levels can occur with concomitant BACTRIM therapy, especially in elderly patients.
Indomethacin | Avoid concurrent use | Increased sulfamethoxazole blood levels may occur in patients who are also receiving indomethacin.
Pyrimethamine | Avoid concurrent use | Occasional reports suggest that patients receiving pyrimethamine as malaria prophylaxis in doses exceeding 25 mg weekly may develop megaloblastic anemia if BACTRIM is prescribed.
Tricyclic; Antidepressants; (TCAs) | Monitor therapeutic response and adjust dose of TCA accordingly | The efficacy of tricyclic antidepressants can decrease when coadministered with BACTRIM.
Oral Hypoglycemics | Monitor blood glucose more frequently | Like other sulfonamide-containing drugs, BACTRIM potentiates the effect of oral hypoglycemic that are metabolized by CYP2C8 (e.g., pioglitazone, repaglinide, and rosiglitazone) or CYP2C9 (e.g., glipizide and glyburide) or eliminated renally via OCT2 (e.g., metformin). Additional monitoring of blood glucose may be warranted.
Amantadine | Avoid concurrent use | In the literature, a single case of toxic delirium has been reported after concomitant intake of BACTRIM and amantadine (an OCT2 substrate). Cases of interactions with other OCT2 substrates, memantine and metformin, have also been reported.
Angiotensin Converting; Enzyme Inhibitors | Avoid concurrent use | In the literature, three cases of hyperkalemia in elderly patients have been reported after concomitant intake of BACTRIM and an angiotensin converting enzyme inhibitor.^5,6
Zidovudine | Monitor for hematologic toxicity | Zidovudine and BACTRIM are known to induce hematological abnormalities. Hence, there is potential for an additive myelotoxicity when coadministered.^7
Dofetilide | Concurrent administration is contraindicated | Elevated plasma concentrations of dofetilide have been reported following concurrent administration of trimethoprim and dofetilide. Increased plasma concentrations of dofetilide may cause serious ventricular arrhythmias associated with QT interval prolongation, including torsade de pointes.^8,9
Procainamide | Closely monitor for clinical and ECG signs of procainamide toxicity and/or procainamide plasma concentration if available | Trimethoprim increases the plasma concentrations of procainamide and its active N-acetyl metabolite (NAPA) when trimethoprim and procainamide are coadministered. The increased procainamide and NAPA plasma concentrations that resulted from the pharmacokinetic interaction with trimethoprim are associated with further prolongation of the QTc interval.^10

Drug/Laboratory Test Interactions

BACTRIM, specifically the trimethoprim component, can interfere with a serum methotrexate assay as determined by the competitive binding protein technique (CBPA) when a bacterial dihydrofolate reductase is used as the binding protein. No interference occurs, however, if methotrexate is measured by a radioimmunoassay (RIA).

The presence of BACTRIM may also interfere with the Jaffé alkaline picrate reaction assay for creatinine, resulting in overestimations of about 10% in the range of normal values.

Carcinogenesis, Mutagenesis, Impairment of Fertility

Carcinogenesis

Sulfamethoxazole was not carcinogenic when assessed in a 26-week tumorigenic mouse (Tg-rasH2) study at doses up to 400 mg/kg/day sulfamethoxazole; equivalent to 2.4-fold the human systemic exposure (at a daily dose of 800 mg sulfamethoxazole twice a day).

Mutagenesis

In vitroreverse mutation bacterial tests according to the standard protocol have not been performed with sulfamethoxazole and trimethoprim in combination. An in vitrochromosomal aberration test in human lymphocytes with sulfamethoxazole and trimethoprim was negative. In in vitroand in vivotests in animal species, sulfamethoxazole and trimethoprim did not damage chromosomes. In vivomicronucleus assays were positive following oral administration of sulfamethoxazole and trimethoprim. Observations of leukocytes obtained from patients treated with sulfamethoxazole and trimethoprim revealed no chromosomal abnormalities.

Sulfamethoxazole alone was positive in an in vitroreverse mutation bacterial assay and in in vitromicronucleus assays using cultured human lymphocytes.

Trimethoprim alone was negative in in vitroreverse mutation bacterial assays and in in vitrochromosomal aberration assays with Chinese Hamster ovary or lung cells with or without S9 activation. In in vitroComet, micronucleus and chromosomal damage assays using cultured human lymphocytes, trimethoprim was positive. In mice following oral administration of trimethoprim, no DNA damage in Comet assays of liver, kidney, lung, spleen, or bone marrow was recorded.

Impairment of Fertility

No adverse effects on fertility or general reproductive performance were observed in rats given oral dosages as high as 350 mg/kg/day sulfamethoxazole plus 70 mg/kg/day trimethoprim, doses roughly two times the recommended human daily dose on a body surface area basis.

Pregnancy

While there are no large, well-controlled studies on the use of sulfamethoxazole and trimethoprim in pregnant women, Brumfitt and Pursell,^11in a retrospective study, reported the outcome of 186 pregnancies during which the mother received either placebo or sulfamethoxazole and trimethoprim. The incidence of congenital abnormalities was 4.5% (3 of 66) in those who received placebo and 3.3% (4 of 120) in those receiving sulfamethoxazole and trimethoprim. There were no abnormalities in the 10 children whose mothers received the drug during the first trimester. In a separate survey, Brumfitt and Pursell also found no congenital abnormalities in 35 children whose mothers had received oral sulfamethoxazole and trimethoprim at the time of conception or shortly thereafter.

Because sulfamethoxazole and trimethoprim may interfere with folic acid metabolism, BACTRIM should be used during pregnancy only if the potential benefit justifies the potential risk to the fetus.

Teratogenic Effects

Human Data

While there are no large prospective, well controlled studies in pregnant women and their babies, some retrospective epidemiologic studies suggest an association between first trimester exposure to sulfamethoxazole and trimethoprim with an increased risk of congenital malformations, particularly neural tube defects, cardiovascular abnormalities, urinary tract defects, oral clefts, and club foot. These studies, however, were limited by the small number of exposed cases and the lack of adjustment for multiple statistical comparisons and confounders. These studies are further limited by recall, selection, and information biases, and by limited generalizability of their findings. Lastly, outcome measures varied between studies, limiting cross-study comparisons. Alternatively, other epidemiologic studies did not detect statistically significant associations between sulfamethoxazole and trimethoprim exposure and specific malformations.

Animal Data

In rats, oral doses of either 533 mg/kg sulfamethoxazole or 200 mg/kg trimethoprim produced teratologic effects manifested mainly as cleft palates. These doses are approximately 5 and 6 times the recommended human total daily dose on a body surface area basis. In two studies in rats, no teratology was observed when 512 mg/kg of sulfamethoxazole was used in combination with 128 mg/kg of trimethoprim. In some rabbit studies, an overall increase in fetal loss (dead and resorbed conceptuses) was associated with doses of trimethoprim 6 times the human therapeutic dose based on body surface area.

Nonteratogenic Effects

See CONTRAINDICATIONSsection.

Nursing Mothers

Levels of sulfamethoxazole and trimethoprim in breast milk are approximately 2–5% of the recommended daily dose for infants over 2 months of age. Caution should be exercised when BACTRIM is administered to a nursing woman, especially when breastfeeding jaundiced, ill, stressed, or premature infants because of the potential risk of bilirubin displacement and kernicterus.

Pediatric Use

BACTRIM is contraindicated for infants younger than 2 months of age (see INDICATIONS AND USAGEand CONTRAINDICATIONSsections).

Geriatric Use

Clinical studies of BACTRIM did not include sufficient numbers of subjects aged 65 and over to determine whether they respond differently from younger subjects.

There may be an increased risk of severe adverse reactions in elderly patients, particularly when complicating conditions exist, e.g., impaired kidney and/or liver function, possible folate deficiency, or concomitant use of other drugs. Severe skin reactions, generalized bone marrow suppression (see WARNINGSand ADVERSE REACTIONSsections), a specific decrease in platelets (with or without purpura), and hyperkalemia are the most frequently reported severe adverse reactions in elderly patients. In those concurrently receiving certain diuretics, primarily thiazides, an increased incidence of thrombocytopenia with purpura has been reported. Increased digoxin blood levels can occur with concomitant BACTRIM therapy, especially in elderly patients. Serum digoxin levels should be monitored. Hematological changes indicative of folic acid deficiency may occur in elderly patients. These effects are reversible by folinic acid therapy. Appropriate dosage adjustments should be made for patients with impaired kidney function and duration of use should be as short as possible to minimize risks of undesired reactions (see DOSAGE AND ADMINISTRATIONsection). The trimethoprim component of BACTRIM may cause hyperkalemia when administered to patients with underlying disorders of potassium metabolism, with renal insufficiency or when given concomitantly with drugs known to induce hyperkalemia, such as angiotensin converting enzyme inhibitors. Close monitoring of serum potassium is warranted in these patients. Discontinuation of BACTRIM treatment is recommended to help lower potassium serum levels. BACTRIM Tablets contain 1.8 mg sodium (0.08 mEq) of sodium per tablet. BACTRIM DS Tablets contain 3.6 mg (0.16 mEq) of sodium per tablet.

Pharmacokinetics parameters for sulfamethoxazole were similar for geriatric subjects and younger adult subjects. The mean maximum serum trimethoprim concentration was higher and mean renal clearance of trimethoprim was lower in geriatric subjects compared with younger subjects (see CLINICAL PHARMACOLOGY: Geriatric Pharmacokinetics).

ADVERSE REACTIONS

The following adverse reactions associated with the use of BACTRIM or sulfamethoxazole and trimethoprim were identified in clinical trials, postmarketing or published reports. Because some of these reactions were reported voluntarily from a population of uncertain size, it is not always possible to reliably estimate their frequency or establish a causal relationship to drug exposure.

The most common adverse reactions are gastrointestinal disturbances (nausea, vomiting, anorexia) and allergic skin reactions (such as rash and urticaria). Fatalities and serious adverse reactions, including severe cutaneous adverse reactions (SCARs), including Stevens-Johnson syndrome, toxic epidermal necrolysis, drug reaction with eosinophilia and systemic symptoms (DRESS), acute febrile neutrophilic dermatosis (AFND), acute generalized erythematous pustulosis (AGEP); fulminant hepatic necrosis; agranulocytosis, aplastic anemia and other blood dyscrasias; acute and delayed lung injury; anaphylaxis and circulatory shock have occurred with the administration of sulfamethoxazole and trimethoprim products, including BACTRIM(see WARNINGS).

Hematologic:Agranulocytosis, aplastic anemia, thrombocytopenia, leukopenia, neutropenia, hemolytic anemia, megaloblastic anemia, hypoprothrombinemia, methemoglobinemia, eosinophilia, thrombotic thrombocytopenic purpura, idiopathic thrombocytopenic purpura.

Allergic/ Immune Reactions:Stevens-Johnson syndrome, toxic epidermal necrolysis, anaphylaxis, allergic myocarditis, erythema multiforme, exfoliative dermatitis, angioedema, drug fever, chills, Henoch-Schoenlein purpura, serum sickness-like syndrome, generalized allergic reactions, generalized skin eruptions, photosensitivity, conjunctival and scleral injection, pruritus, urticaria, rash, periarteritis nodosa, hemophagocytic lymphohistiocytosis (HLH), systemic lupus erythematosus, drug reaction with eosinophilia and systemic symptoms (DRESS), acute generalized erythematous pustulosis (AGEP), and acute febrile neutrophilic dermatosis (AFND) (see WARNINGS).

Gastrointestinal:Hepatitis (including cholestatic jaundice and hepatic necrosis), elevation of serum transaminase and bilirubin, pseudomembranous enterocolitis, pancreatitis, stomatitis, glossitis, nausea, emesis, abdominal pain, diarrhea, anorexia.

Genitourinary:Renal failure, interstitial nephritis, BUN and serum creatinine elevation, renal insufficiency, oliguria and anuria, crystalluria and nephrotoxicity in association with cyclosporine.

Metabolic and Nutritional:Hyperkalemia, hyponatremia (see PRECAUTIONS: Electrolyte Abnormalities), metabolic acidosis.

Neurologic:Aseptic meningitis, convulsions, peripheral neuritis, ataxia, vertigo, tinnitus, headache.

Psychiatric:Hallucinations, depression, apathy, nervousness.

Endocrine:The sulfonamides bear certain chemical similarities to some goitrogens, diuretics (acetazolamide and the thiazides) and oral hypoglycemic agents. Cross-sensitivity may exist with these agents. Diuresis and hypoglycemia have occurred.

Musculoskeletal:Arthralgia, myalgia, rhabdomyolysis.

Respiratory:Cough, shortness of breath and pulmonary infiltrates, acute eosinophilic pneumonia, acute and delayed lung injury, interstitial lung disease, acute respiratory failure (see WARNINGS).

Cardiovascular System:QT prolongation resulting in ventricular tachycardia and torsades de pointes, circulatory shock (see WARNINGS) .

Miscellaneous:Weakness, fatigue, insomnia.

OVERDOSAGE

Acute

The amount of a single dose of BACTRIM that is either associated with symptoms of overdosage or is likely to be life-threatening has not been reported. Signs and symptoms of overdosage reported with sulfonamides include anorexia, colic, nausea, vomiting, dizziness, headache, drowsiness and unconsciousness. Pyrexia, hematuria and crystalluria may be noted. Blood dyscrasias and jaundice are potential late manifestations of overdosage.

Signs of acute overdosage with trimethoprim include nausea, vomiting, dizziness, headache, mental depression, confusion and bone marrow depression.

General principles of treatment include the institution of gastric lavage or emesis, forcing oral fluids, and the administration of intravenous fluids if urine output is low and renal function is normal. Acidification of the urine will increase renal elimination of trimethoprim. The patient should be monitored with blood counts and appropriate blood chemistries, including electrolytes. If a significant blood dyscrasia or jaundice occurs, specific therapy should be instituted for these complications. Peritoneal dialysis is not effective and hemodialysis is only moderately effective in eliminating sulfamethoxazole and trimethoprim.

Chronic

Use of BACTRIM at high doses and/or for extended periods of time may cause bone marrow depression manifested as thrombocytopenia, leukopenia and/or megaloblastic anemia. If signs of bone marrow depression occur, the patient should be given leucovorin 5 to 15 mg daily until normal hematopoiesis is restored.

DOSAGE AND ADMINISTRATION

BACTRIM is contraindicated in pediatric patients less than 2 months of age.

Urinary Tract Infections and Shigellosis in Adults and Pediatric Patients, and Acute Otitis Media in Children

Adults:The usual adult dosage in the treatment of urinary tract infections is 1 BACTRIM DS (double strength) tablet or 2 BACTRIM tablets every 12 hours for 10 to 14 days. An identical daily dosage is used for 5 days in the treatment of shigellosis.

Children:The recommended dose for children with urinary tract infections or acute otitis media is 40 mg/kg sulfamethoxazole and 8 mg/kg trimethoprim per 24 hours, given in two divided doses every 12 hours for 10 days. An identical daily dosage is used for 5 days in the treatment of shigellosis. The following table is a guideline for the attainment of this dosage:

Children 2 months of age or older:
Weight |  | Dose–every 12 hours
lb | kg | Tablets
22 | 10 | –
44 | 20 | 1
66 | 30 | 1½
88 | 40 | 2 or 1 DS tablet

For Patients with Impaired Renal Function

When renal function is impaired, a reduced dosage should be employed using the following table:

Creatinine Clearance (mL/min) | Recommended Dosage Regimen
Above 30 | Usual standard regimen
15–30 | ½ the usual regimen
Below 15 | Use not recommended

Acute Exacerbations of Chronic Bronchitis in Adults
The usual adult dosage in the treatment of acute exacerbations of chronic bronchitis is 1 BACTRIM DS (double strength) tablet or 2 BACTRIM tablets every 12 hours for 14 days.

Pneumocystis jiroveciiPneumonia
Treatment

Adults and Children:
The recommended dosage for treatment of patients with documented Pneumocystis jiroveciipneumonia is 75 to 100 mg/kg sulfamethoxazole and 15 to 20 mg/kg trimethoprim per 24 hours given in equally divided doses every 6 hours for 14 to 21 days.^12The following table is a guideline for the upper limit of this dosage:

Weight |  | Dose–every 6 hours
lb | kg | Tablets
18 | 8 | –
35 | 16 | 1
53 | 24 | 1½
70 | 32 | 2 or 1 DS tablet
88 | 40 | 2½
106 | 48 | 3 or 1½ DS tablets
141 | 64 | 4 or 2 DS tablets
176 | 80 | 5 or 2½ DS tablets

For the lower limit dose (75 mg/kg sulfamethoxazole and 15 mg/kg trimethoprim per 24 hours) administer 75% of the dose in the above table.

Prophylaxis
Adults:

The recommended dosage for prophylaxis in adults is 1 BACTRIM DS (double strength) tablet daily.^13

Children:
For children, the recommended dose is 750 mg/m^2/day sulfamethoxazole with 150 mg/m^2/day trimethoprim given orally in equally divided doses twice a day, on 3 consecutive days per week. The total daily dose should not exceed 1600 mg sulfamethoxazole and 320 mg trimethoprim.^14The following table is a guideline for the attainment of this dosage in children:

Body Surface Area | Dose–every 12 hours
(m^2) | Tablets
0.26 | –
0.53 | ½
1.06 | 1

Traveler’s Diarrhea in Adults
For the treatment of traveler’s diarrhea, the usual adult dosage is 1 BACTRIM DS (double strength) tablet or 2 BACTRIM tablets every 12 hours for 5 days.

HOW SUPPLIED

BACTRIM Tablets are supplied as follows:

BACTRIM DS (double strength) Tablets (white, oval shaped, scored) containing 160 mg trimethoprim and 800 mg sulfamethoxazole – bottles of 100 (NDC 49708-146-01). Imprint on tablets (debossed): (front) BACTRIM DS

BACTRIM Tablets (white, round, scored) containing 80 mg trimethoprim and 400 mg sulfamethoxazole – bottles of 100 (NDC 49708-145-01). Imprint on tablets (debossed): (front) BACTRIM

Store at 20° to 25°C (68° to 77°F).
[See USP Controlled Room Temperature]

DISPENSE IN TIGHT, LIGHT-RESISTANT CONTAINER.

REFERENCES

1. Kremers P, Duvivier J, Heusghem C. Pharmacokinetic Studies of Co-Trimoxazole in Man after Single and Repeated Doses. J Clin Pharmacol. Feb-Mar 1974; 14:112–117.
2. Kaplan SA, et al. Pharmacokinetic Profile of Trimethoprim-Sulfamethoxazole in Man. J Infect Dis. Nov 1973; 128 (Suppl): S547–S555.
3. Varoquaux O, et al. Pharmacokinetics of the trimethoprim-sulfamethoxazole combination in the elderly. Br J Clin Pharmacol. 1985; 20:575–581.
4. Safrin S, Lee BL, Sande MA. Adjunctive folinic acid with trimethoprim-sulfamethoxazole for Pneumocystis cariniipneumonia in AIDS patients is associated with an increased risk of therapeutic failure and death. J Infect Dis. 1994 Oct;170(4):912–7.
5. Marinella Mark A. 1999. Trimethoprim-induced hyperkalemia: An analysis of reported cases. Gerontol. 45:209–212.
6. Margassery, S. and B. Bastani. 2002. Life threatening hyperkalemia and acidosis secondary to trimethoprim-sulfamethoxazole treatment. J. Nephrol. 14:410–414.
7. Moh R, et al. Haematological changes in adults receiving a zidovudine-containing HAART regimen in combination with cotrimoxazole in Côte d’Ivoire. Antivir Ther. 2005;10(5):615-24.
8. Al-Khatib SM, LaPointe N, Kramer JM, Califf RM. What Clinicians Should Know About the QT Interval. JAMA. 2003;289(16):2120-2127.
9. Boyer EW, Stork C, Wang RY. Review: The Pharmacology and Toxicology of Dofetilide. Int J Med Toxicol.2001;4(2):16.
10. Kosoglou T, Rocci ML Jr, Vlasses PH. Trimethoprim alters the disposition of procainamide and N-acetylprocainamide. Clin Pharmacol Ther. Oct 1988;44(4):467-77.
11. Brumfitt W, Pursell R. Trimethoprim/Sulfamethoxazole in the Treatment of Bacteriuria in Women. J Infect Dis. Nov 1973; 128 (Suppl): S657–S663.
12. Masur H. Prevention and treatment of Pneumocystispneumonia. N Engl J Med. 1992; 327: 1853–1880.
13. Recommendations for prophylaxis against Pneumocystis cariniipneumonia for adults and adolescents infected with human immunodeficiency virus. MMWR.1992; 41(RR–4):1–11.
14. CDC Guidelines for prophylaxis against Pneumocystis cariniipneumonia for children infected with human immunodeficiency virus. MMWR. 1991; 40(RR–2):1–13.

All trademarks are property of their respective owners.

© 2024 Sun Pharmaceutical Industries, Inc. All rights reserved.

Distributed by:

Sun Pharmaceutical Industries, Inc.

Cranbury, NJ 08512

Rev. 08, December 2024